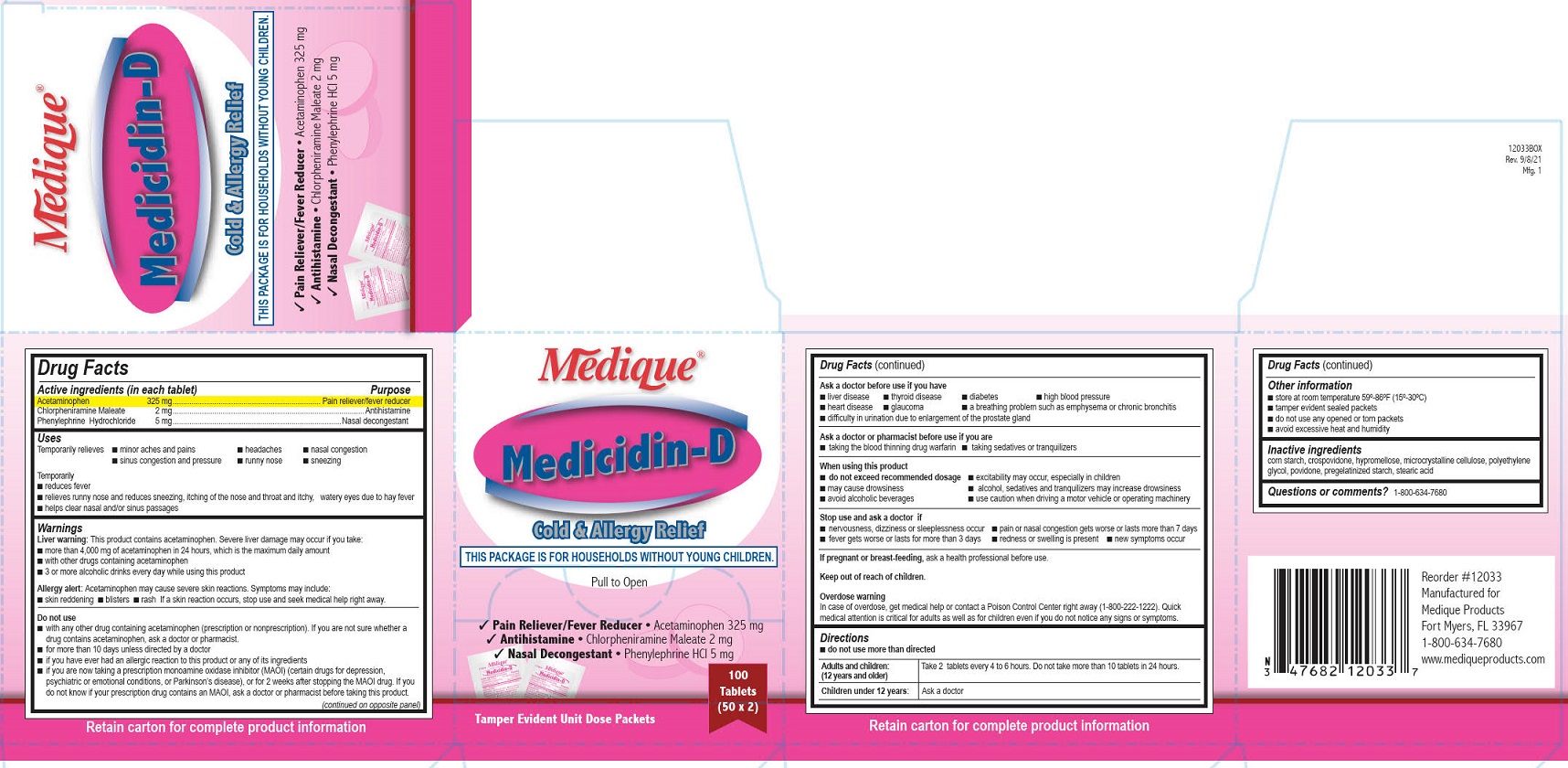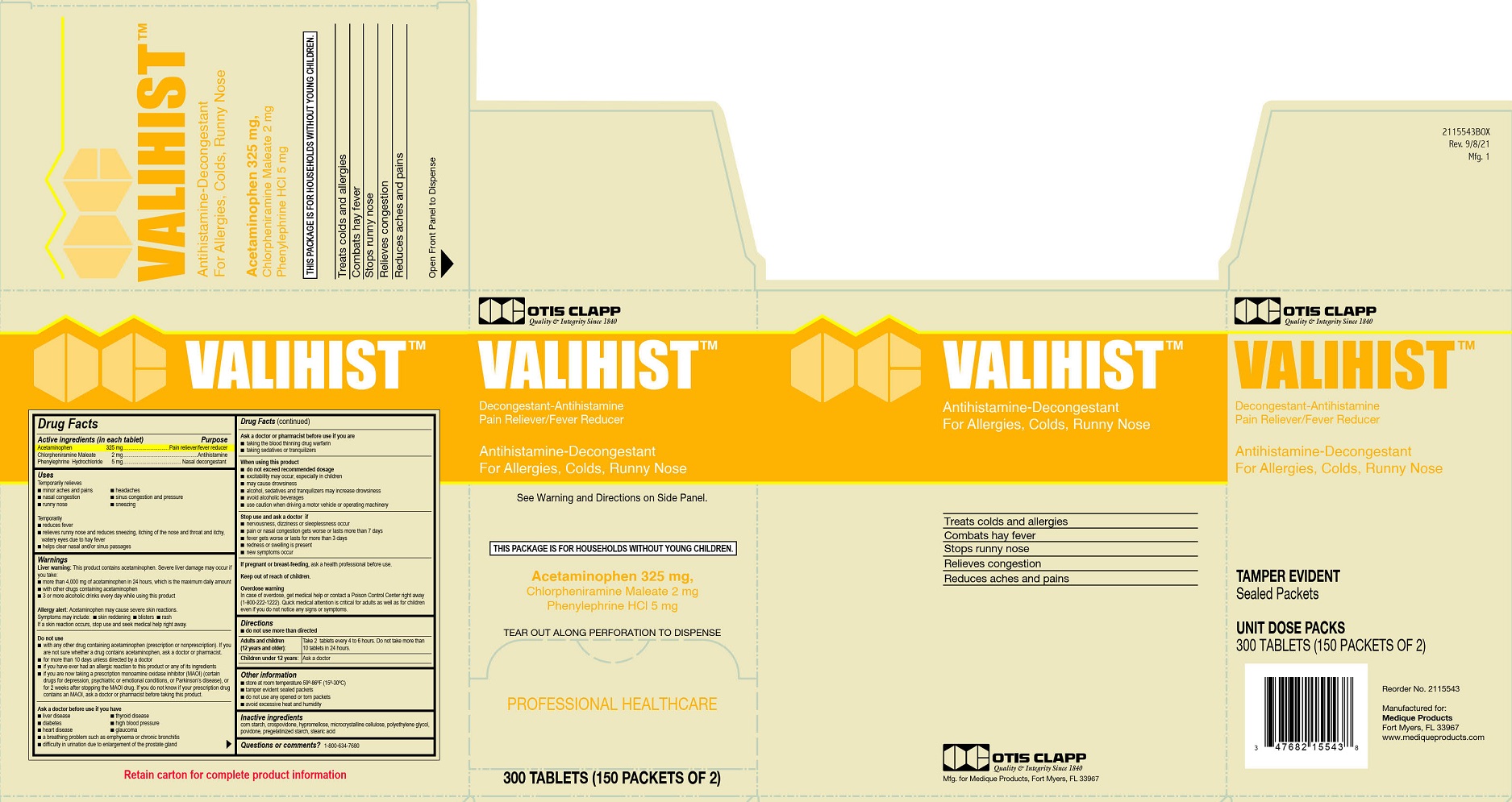 DRUG LABEL: Otis Clapp Valihist
NDC: 47682-543 | Form: TABLET, FILM COATED
Manufacturer: Unifirst First Aid Corporation
Category: otc | Type: HUMAN OTC DRUG LABEL
Date: 20250908

ACTIVE INGREDIENTS: ACETAMINOPHEN 325 mg/1 1; CHLORPHENIRAMINE MALEATE 2 mg/1 1; PHENYLEPHRINE HYDROCHLORIDE 5 mg/1 1
INACTIVE INGREDIENTS: CELLULOSE, MICROCRYSTALLINE; HYPROMELLOSES; POLYETHYLENE GLYCOL, UNSPECIFIED; STARCH, CORN; STEARIC ACID; CROSPOVIDONE; POVIDONE

Medique Medicidin D/ Otis Clapp Valihist

Drug Facts

Active ingredients (in each tablet)

Acetaminophen 325 mg

Chlorpheniramine Maleate 2 mg

Phenylephrine Hydrochloride 5 mg

Purpose

Pain reliever/fever reducer

Antihistamine

Nasal decongestant

Uses

Temporarily relieves

- minor aches and pains
- headache
- nasal congestion
- sinus congestion and pressure
- runny nose
- sneezing

Temporarily

- reduces fever
- relieves runny nose and reduces sneezing, itching of the nose and throat and itchy, watery eyes due to hay fever
- helps clear nasal and/or sinus passages

Warnings

Liver warning: This product contains acetaminophen. Severe liver damage may occur if you take:

- more than 4,000 mg of acetaminophen in 24 hours, which is the maximum daily amount
- with other drugs containing acetaminophen
- 3 or more alcoholic drinks every day while using this product

Allergy alert: Acetaminophen may cause severe skin reactions. Symptoms may include:

- skin reddening
- blisters
- rash

If a skin reaction occurs, stop use and seek medical help right away.

Do not use

- with any other drug containing acetaminophen (prescription or nonprescription). If you are not sure whether a drug contains acetaminophen, ask a doctor or pharmacist.
- for more than 10 days for pain unless directed by a doctor
- if you ever had an allergic reaction to this product or any of its ingredients
- if you are now taking a prescription monoamine oxidase inhibitor (MAOI) (certain drugs for depression, psychiatric or emotional conditions, or Parkinson's disease), or for 2 weeks after stopping the MAOI drug. If you do not know if your prescription drug contains an MAOI, ask a doctor or pharmacist before taking this product.

Ask a doctor before use if you have

liver disease
thyroid disease
diabetes
high blood pressure
heart disease
glaucoma
chronic bronchitis or emphysema
difficulty in urination due to enlargement of the prostate gland

Ask a doctor or pharmacist before use if you are

- taking the blood thinning drug warfarin
- taking sedatives or tranquilizers

When using this product

- do not exceed recommended dosage
- excitability may occur, especially in children
- may cause drowsiness
- alcohol, sedatives and tranquilizers may increase drowsiness
- avoid alcoholic beverages
- use caution when driving a motor vehicle or operating machinery

Stop use and ask a doctor if

- nervousness, dizziness or sleeplessness occur
- pain or nasal congestion gets worse or lasts more than 7 days
- fever gets worse or lasts more than 3 days
- redness or swelling is present
- new symptoms occur

PREGNANCY OR BREAST FEEDING

If pregnant or breast-feeding, ask a health professional before use.

Keep out of reach of children.

Overdose warning

In case of overdose, get medical help or contact a Poison Control Center right away (1-800-222-12220. Quick medical attention is critical for adults as well as for children even if you do not notice any signs or symptoms.

Directions

- do not use more than directed

Adults and children (12 years and older): Take 2 tablets every 4 to 6 hours. Do not take more than 10 tablets in 24 hours.

Children under 12 years: Ask a doctor

Other information

- store at room temperature 59º-86ºF (15º-30ºC)
- tamper evident sealed packets
- do not use any opened or torn packets
- avoid excessive heat and humidity

Inactive ingredients

corn starch, crospovidone, hypromellose, microcrystalline cellulose, polyethylene glycol, povidone, pregelatinized starch, stearic acid

Questions or comments? 1-800-634-7680

Principal Display Panel - Otis Clapp Valihist Label

Otis Clapp

Quality and Integrity Since 1840

VALIHIST ™

Decongestant-Antihistamine

Pain Reliever-Fever Reducer

Antihistamine- Decongestant

For Allergies, Colds, Runny Nose

See Warnings and Directions on Side Panel

This Package is for Households without Young Children.

Acetaminophen 325 mg,

Chlorpheniramine Maleate 2mg

Phenylephrine HCl 5 mg

Tear Out Along Perforation To Dispense

PROFESSIONAL HEALTHCARE

300 TABLETS (150 PACKETS OF 2)

Principal Display Panel - Medique Medicidin D Label

Medique®

Medicidin-D

Cold and Allergy Relief

This Package is for Households without Young Children.

Pull to Open

Pain Reliever/ Fever Reducer ● Acetaminophen 325mg

Antihistamine ● Chlorpheniramine Maleate 2mg

Nasal Decongestant ● Phenylephrine HCl 5mg

100Tablets

(50 x 2)

Tamper Evident Unit Dose Packets